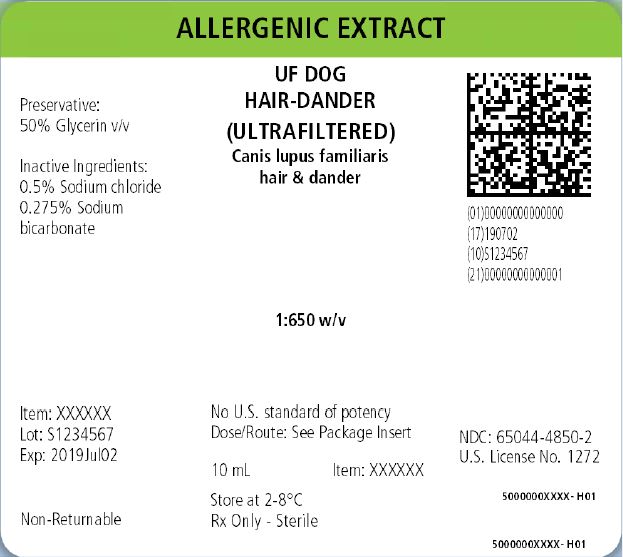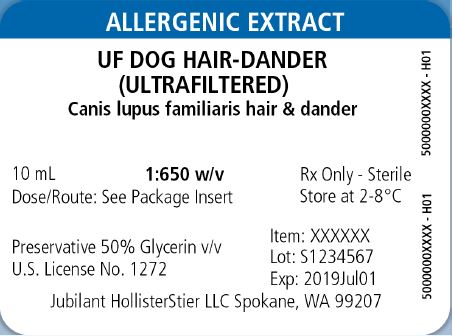 DRUG LABEL: Animal Allergens, AP Cattle Hair and Dander
NDC: 65044-4811 | Form: INJECTION, SOLUTION
Manufacturer: Jubilant HollisterStier LLC
Category: other | Type: NON-STANDARDIZED ALLERGENIC LABEL
Date: 20251119

ACTIVE INGREDIENTS: BOS TAURUS HAIR 0.01 g/1 mL; BOS TAURUS DANDER 0.01 g/1 mL
INACTIVE INGREDIENTS: GLYCERIN; SODIUM CHLORIDE; SODIUM BICARBONATE

HIGHLIGHTS OF PRESCRIBING INFORMATION

These highlights do not include all the information needed to use NON‑STANDARDIZED ALLERGENIC EXTRACTS (POLLENS, MOLDS, EPIDERMALS AND INSECTS) safely and effectively. See full prescribing information for NON-STANDARDIZED ALLERGENIC EXTRACTS (POLLENS, MOLDS, EPIDERMALS AND INSECTS).
NON-STANDARDIZED ALLERGENIC EXTRACTS (POLLENS, MOLDS, EPIDERMALS AND INSECTS)
Solution for percutaneous, intradermal, or subcutaneous administration Initial U.S. Approval: 1925

WARNING: ANAPHYLAXIS

See full prescribing information for complete boxed warning.

- Non-standardized allergenic extracts can cause anaphylaxis, including anaphylactic shock and death.(5.1)
- Do not administer to individuals with severe, unstable or uncontrolled asthma, history of severe systemic reaction to the allergen extract when administered for diagnosis or treatment, or with medical conditions that reduce the ability to survive anaphylaxis.(4)
- Observe individuals for at least 30 minutes following administration.Emergency measures and personnel trained in their use must be available in the event of a life-threatening reaction.(5.1)
- Individuals with extreme sensitivity to these products, on an accelerated immunotherapy build-up, switching to another lot, receiving high doses of these products, or exposed to similar allergens may be at increased risk of anaphylaxis.(5.1)
- These products may not be suitable for individuals who may be unresponsive to epinephrine or inhaled bronchodilators, such as those taking beta-blockers.(5.1)

1 INDICATIONS AND USAGE

Non-standardized allergenic extracts are indicated for:

- Skin test diagnosis of patients with a clinical history of allergy to the specific corresponding allergens.(1)
- Immunotherapy for the reduction of allergen-induced allergic symptoms confirmed by positive skin test or by in vitro testing for allergen-specific IgE antibodies.(1)

2 DOSAGE AND ADMINISTRATION

For percutaneous, intradermal, or subcutaneous use only.

Administration:

- Percutaneous for diagnostic testing.
- Intradermal for diagnostic testing.
- Subcutaneous for immunotherapy.

See full prescribing information for details on dosing and dilution preparation. (2)

3 DOSAGE FORMS AND STRENGTHS

Non-standardized allergenic extract solutions: stock concentrates, labeled in weight/volume, in a glycerin-preserved extracting fluid, supplied in 5, 10, 30, and 50 mL vials. (3, 16) Refer to the vial label for the product concentration. (11)

4 CONTRAINDICATIONS

- Severe, unstable or uncontrolled asthma.(4)
- History of any severe systemic reaction to the allergen extract when administered for diagnosis or treatment.(4)
- Medical conditions that reduce the ability to survive anaphylaxis.(4)

5 WARNINGS AND PRECAUTIONS

The risk of anaphylaxis may be increased in the following situations:

- Extreme sensitivity to non-standardized allergenic extracts.
- Concomitant environmental exposure to similar allergens.
- Receipt of high concentrations and volumes of non-standardized allergenic extracts.
- Receipt of an accelerated build-up schedule (e.g., "rush" immunotherapy).
- Changing to another lot of allergen.(5)

6 ADVERSE REACTIONS

Common adverse reactions reported for non-standardized allergenic extracts are:

- Local adverse reactions, occurring in 26 to 82% of all patients who receive subcutaneous immunotherapy (e.g., erythema, swelling, pruritus, tenderness and pain at the injection site).(6)
- Systemic adverse reactions, occurring in ≤ 7% of patients who receive subcutaneous immunotherapy (e.g., generalized skin erythema, urticaria, pruritus, angioedema, rhinitis, wheezing, laryngeal edema, and hypotension).Systemic reactions may be fatal.(6)

To report SUSPECTED ADVERSE REACTIONS, contact Jubilant HollisterStier at 1-800-495-7437 or Adverse.Reactions@jhs.jubl.com; or the FDA at 1-800-FDA-1088 or www.fda.gov/medwatch.

7 DRUG INTERACTIONS

- Certain medications may decrease skin test wheal and erythema responses, including antihistamines, topical corticosteroids, topical anesthetics, and tricyclic antidepressants.(7)

FULL PRESCRIBING INFORMATION

WARNING: ANAPHYLAXIS

- Non-standardized allergenic extracts can cause anaphylaxis, including anaphylactic shock and death.(5.1)
- Do not administer to individuals with:
  - severe, unstable or uncontrolled asthma;
  - history of severe systemic reaction to the allergen extract when administered for diagnosis of treatment;
  - medical conditions that reduce the ability to survive anaphylaxis.(4)
- Observe individuals for at least 30 minutes following administration. Emergency measures and personnel trained in their use must be available in the event of a life-threatening reaction.(5.1)
- Individuals with extreme sensitivity to these products, on an accelerated immunotherapy build-up, switching to another lot, receiving high doses of these products, or exposed to similar allergens may be at increased risk of anaphylaxis.(5.1)
- These products may not be suitable for individuals who may be unresponsive to epinephrine or inhaled bronchodilators, such as those taking beta-blockers.(5.1)

1 INDICATIONS AND USAGE

NON-STANDARDIZED ALLERGENIC EXTRACTS are indicated for:

- Skin test diagnosis of individuals with a clinical history of allergy to the specific corresponding allergens.

NON-STANDARDIZED ALLERGENIC EXTRACTS are indicated for:

- Immunotherapy for the reduction of allergen-induced allergic symptoms confirmed by positive skin test or by in vitro testing for allergen specific IgE antibodies for the specific corresponding allergens.

2 DOSAGE AND ADMINISTRATION

For percutaneous, intradermal, or subcutaneous administration only. Do not inject intravenously.

2.1 Preparation for Administration

Appearance is clear to slightly opalescent. Parenteral drug products should be inspected visually for particulate matter and discoloration prior to administration, whenever solution and container permit. Discard solution if either of these conditions exist.

Non-standardized allergenic extracts diluted with Albumin Saline with Phenol (0.4%) (stabilized diluent) may be more potent than extracts diluted with diluents that do not contain albumin. When switching from non-stabilized to stabilized diluent, consider less concentrated initial dilutions for both intradermal testing and immunotherapy.

Different formulations, preparations, or new lots of non-standardized allergenic extracts are not interchangeable. Dosing should be adjusted appropriately when formulations, preparations, or lots of non-standardized allergenic extracts are changed [see Immunotherapy (2.3) and Dosage Forms and Strengths (3)].

Allergenic extracts may be prepared for intradermal (diagnosis) or subcutaneous (immunotherapy) administration by diluting stock concentrates.

- For diluent, use sterile albumin saline with phenol or sterile normal saline with phenol.
- Dilute stock concentrates by a minimum of 100-fold for intradermal testing. Dilutions of 1,000-fold or greater are appropriate starting points for patients with a clinical history of adverse reaction.

To prepare dilutions for intradermal testing and immunotherapy, start with a stock concentrate, and prepare a ten-fold (1:10) dilution by adding 0.5 mL of concentrate to 4.5 mL of sterile aqueous diluent. Prepare subsequent dilutions in a similar manner. (see Table 1).

Table 1: 10-fold Dilution Series

Dilution | Extract | Milliliters of Diluent | Dilution Strength (w/v) | Dilution Strength (w/v) | Dilution Strength (w/v) | Dilution Strength (w/v) | Dilution Strength (w/v)
0 | Concentrate |  | 1:10 | 1:20 | 1:50 | 1:100 | 1:650
1 | 0.5 mL Concentrate | 4.5 | 1:100 | 1:200 | 1:500 | 1:1,000 | 1:6,500
2 | 0.5 mL Dilution | 4.5 | 1:1,000 | 1:2,000 | 1:5,000 | 1:10,000 | 1:65,000
3 | 0.5 mL Dilution 2 | 4.5 | 1:10,000 | 1:20,000 | 1:50,000 | 1:100,000 | 1:650,000
4 | 0.5 mL Dilution 3 | 4.5 | 1:100,000 | 1:200,000 | 1:500,000 | 1:1,000,000 | 1:6,500,000
5 | 0.5 mL Dilution 4 | 4.5 | 1:1,000,000 | 1:2,000,000 | 1:5,000,000 | 1:10,000,000 | 1:65,000,000
6 | 0.5 mL Dilution 5 | 4.5 | 1:10,000,000 | 1:20,000,000 | 1:50,000,000 | 1:100,000,000 | 1:650,000,000
Note: A lower starting dose and/or less concentrated dilutions may be necessary for highly sensitive patients with a clinical history of sensitivity, or for those who display severe symptoms. [see Diagnostic Testing (2.2), Percutaneous Skin Testing (2.2.1) and Intradermal (Intracutaneous) Skin Test (2.2.2)].

2.2 Diagnostic Testing

Testing is performed to identify patients that exhibit an allergic response at the site of administration. False positive reactions may occur. A positive skin test reaction must be interpreted in the context of the individual’s clinical history and known exposure to the allergen.

- Administer percutaneous tests prior to administration of intradermal tests to identify highly sensitive patients.
- Do not use allergen mixes for diagnostic testing because a positive reaction would not permit specific identification of the allergen(s) that elicited the reaction. In addition, a negative reaction would fail to indicate whether an individual component allergen would have elicited a positive reaction at full strength.

2.2.1 Percutaneous Skin Testing

Dose

Unless an individual is suspected to be at greater risk for anaphylaxis, the initial starting dose is 1 drop (approximately 0.05 mL) of undiluted allergenic extract. For individuals suspected to be at greater risk for anaphylaxis (for example, as indicated by a history of allergen-induced anaphylaxis), initiate percutaneous testing with a sequence of serial 10-fold dilutions of undiluted allergenic extract spaced 15‑20 minutes apart [see Preparation for Administration (2.1)].

Administration

- Percutaneous Test: Place one drop (approximately 0.05 mL) of allergen on the skin and pierce through drop superficially into the skin, lifting slightly. Use a skin test device, such as a sterile needle, lancet, or bifurcated needle.
- Percutaneous Test using self-loading devices: Refer to the manufacturer’s product instructions.

Concurrently, use a positive histamine skin test control to identify patients whose recent use of drugs with antihistamine activity may result in a false negative skin test. Apply a 50% glycerin solution as a negative control, to identify false positive responses to the extracting fluid used in the manufacture of allergenic extracts, or due to dermographism [see Drug Interactions (7)].

Interpreting Results

For interpretation of percutaneous skin tests, refer to the information provided in Allergy Diagnostic Testing: An Updated Practice Parameter.^1 In addition, follow the directions provided with the percutaneous skin test devices. Measure wheal responses for the histamine positive control test at 15 minutes and for the allergen tests at 15 to 20 minutes.

- The negative control (50% glycerin solution) response should measure < 3 mm wheal and ≤ 10 mm flare.^1
- Response to positive controls should be at least 3 millimeters larger than the response to the negative control.
- If either the response to the histamine positive control or to the negative control do not meet the criteria above for acceptable wheal size, the results for the allergenic extracts tested at the same time should be considered invalid and be repeated.
- Fire Ant: Percutaneous testing is considered positive when the response occurs at a concentration of 1:100 w/v or less.^4

2.2.2 Intradermal (Intracutaneous) Skin Test

Always perform percutaneous tests prior to intradermal skin tests.^(1, 2)

Dose

Perform intradermal tests with at least 100-fold less concentrated solutions than the stock concentrates used in percutaneous tests [see Preparation and Administration (2.1)].

Fire Ant: Use 0.02 mL of a 1:100,000 v/v dilution of the concentrate for intradermal tests. Very sensitive individuals such as those who have had nearly fatal anaphylactic reactions may not tolerate even 1:100,000 v/v dilution of concentrate as a starting point. These patients should be tested with a 1:10,000,000 v/v dilution of concentrate [see Preparation for Administration (2.1)].

Use intradermal tests following a negative or equivocal percutaneous test when the patient continues to report a history of symptoms following exposure to a specific allergen.

Administration

Intradermally inject 0.02 mL of the allergen using a 1 mL intradermal testing syringe with a 26 or 27 gauge, 1/2" or 3/8" needle with intradermal bevel, graduated in 0.01 units. Insert needle at a 30˚ angle, bevel down.

Test concurrently with a positive histamine control at intradermal strength (0.1 mg/mL of histamine base) and an aqueous buffer negative control (Sterile Albumin Saline with Phenol, Sterile Buffered Saline with Phenol).

Interpreting Results

For interpretation of intradermal skin tests, follow the information provided in Allergy Diagnostic Testing: An Updated Practice Parameter.^1

- Measure wheal responses for the histamine positive control test and allergen tests at 10‑15 minutes after injection
- Response to the positive control should be at least 3 millimeters larger than the response to the negative control.
- The negative control (50% glycerin solution) response should measure < 3‑mm wheal and ≤ 10 mm flare (erythema).
- If either the response to the histamine positive control or to the negative control do not meet the criteria above for acceptable wheal size, the results for the allergenic extracts tested at the same time should be considered invalid and be repeated.
- Fire Ant: Intradermal testing is considered positive when the response occurs at a concentration of 1:1,000 w/v or less.^4

2.3 Immunotherapy

For subcutaneous administration only.

Administration of Immunotherapy

Administer immunotherapy by subcutaneous injection in the lateral aspect of the arm or thigh. Avoid injection directly into any blood vessels. Administer injections with a sterile 1 mL allergy treatment syringe with a 26 or 27 gauge, 1/2", beveled needle, graduated in 0.01 units.

The optimal interval between doses of allergenic extract varies among individuals. Injections are usually given one or two times per week until the maintenance dose is reached, at which time the injection interval is increased to 2, 3, and finally 4 weeks.

Most adverse reactions occur within 30 minutes after injection. Therefore, observe patients for at least 30 minutes. For high risk patients, 30 minutes of observation may not be sufficient.^2

Dosing of non-standardized allergenic extracts for allergen immunotherapy is highly individualized. Adjust dose according to the degree of sensitivity of the patient, tolerance to the extract administered during the early phases of an injection regimen, and the clinical response. Dosing is individualized by choice of an initial dose, the schedule of dose build-up, the target maintenance dose, the actual maintenance dose, and the duration of treatment.

The large volume of solution for immunotherapy may produce increased discomfort in the pediatric population. In order to achieve the total dose required, the volume of the dose may need to be divided into more than one injection per visit.²

2.3.1 Dose Build-up

Following the first administration of 0.03 mL of the selected initial dilution of allergenic extract, dosing is increased in 0.03 mL to 0.12 mL increments until 0.3 mL is reached, following which 0.03 mL is administered from the next most concentrated allergen extract or allergen mixture vial in the dilution series. The interval between doses is usually 3 to 7 days during dose build-up. Proceed in this manner until a maintenance dose is reached. The final maintenance dose may not be the target maintenance dose selected at the beginning of therapy.

The following adjustments may be necessary during dose build-up:

- If allergic symptoms or local reactions develop shortly after dose administration, decrease the dose volume to one-half or one-quarter of the maximum dose previously attained.
- If the patient is experiencing any seasonal allergy symptoms, decrease the dose volume to one-half or one‑quarter of the maximum dose previously attained.
- Adjust the dose periodically based on the patient’s tolerance and reaction.
- Decrease the dose if the previous injection resulted in a marked local reaction.
- Repeat the previous dose or reduce the dose at the next administration if local reactions persist for longer than 24 hours.
- Decrease the dose if the previous injection resulted in a systemic reaction.Any evidence of a systemic reaction is an indication for a significant (at least 75%) reduction in the subsequent dose or the cessation of immunotherapy.
- Repeated systemic reactions, however mild, are sufficient reason for the cessation of further attempts to increase the reaction-causing dose.

2.3.2 Maintenance Dose Selection, Adjustments, and Intervals

The maintenance dose is the dose that provides therapeutic efficacy without severe adverse local or systemic reactions. This dose may be limited by adverse reactions and may not be the original targeted maintenance dose. Select a maintenance dose based on the patient's clinical response and tolerance.

- Suggested maintenance dose is 0.3 mL of the undiluted allergen extract. Occasionally, higher doses are necessary to relieve symptoms.
- Maintenance doses larger than 0.3 mL of undiluted allergen extract may cause patient discomfort due to the 50% glycerin content.
- After the maintenance dose is achieved, increase the injection interval to 2 weeks, then 3 weeks, and finally 4 weeks, as tolerated. Administer the maintenance dose at a given interval three or four times before further increasing the interval to assure that no reactions occur. Protection may be lost rapidly if the interval between doses is more than 4 weeks.

The following adjustments to the maintenance dose may be necessary.

Withhold immunotherapy and/or reduce dosage, if any of the following conditions exist:

- Severe symptoms of rhinitis and/or asthma. Decrease dose to one-half or one-quarter of the maximum dose previously attained if the patient has any seasonal symptoms.
- Allergic symptoms or a local reaction following the prior dose.
- Infection accompanied by fever.
- Exposure to excessive amounts of clinically relevant allergen prior to a scheduled injection.

In situations prompting dose reduction, a cautious increase in dosage can be attempted once the reduced dose is tolerated.

Decrease the interval between doses if symptoms develop before the next injection is scheduled.

In some patients, the dosage may be increased and/or the dosing interval shortened based on individual responses and dosing requirements. If the onset of symptoms is soon after the initiation of immunotherapy, decrease the interval between each dose.

Changing to a different lot of extract: All extracts can lose allergenic activity over time and extracts vary in allergenic activity. Two different lots of extract could differ substantially in allergenic activity, even if they are the same formula and concentration. The volume of the first dose from the new vial should not exceed 50% of the previous dose. Do not use extracts beyond their expiry date.

Changing to a different formulation of extract or to an extract from a different manufacturer: Decrease the starting dose of the new extract when the extract is the same formula and dilution as the one previously used. In general, a volume dose reduction to 50% of the previous product dose is adequate, but each situation must be evaluated separately considering the patient's history of sensitivity, tolerance of previous injections, and other factors. If the patient tolerates the 50% decrease, then raise the next dose to the previous tolerated dose amount. To re-establish the maintenance dose the starting interval between doses should not be greater than one week.

Prolonged period has elapsed since the last injection: Patients may lose tolerance for allergen injections during prolonged intervals (> 4 weeks) between doses. The duration of tolerance is an individual characteristic and varies from patient to patient. In general, the longer the lapse in the injection schedule, the greater dose reduction required.

Changes made in the extract concentrate formula: Changes other than those listed above such as a difference in extracting fluid (e.g., change from non-glycerin extracts to 50% glycerin extracts), combining two or more stock concentrates, or any other change can affect a patient’s tolerance of the treatment. Extra dilutions are recommended whenever starting a revised formula. The greater the change, the greater the number of dilutions required.

Duration of Treatment

The duration of treatment for immunotherapy has not been established. A period of two to three years of injection therapy constitutes an average minimum course of treatment. Evaluate patients for treatment response at least every 6 to 12 months while they receive immunotherapy.

3 DOSAGE FORMS AND STRENGTHS

Non-standardized allergenic extracts are solutions: stock concentrates, labeled in weight/volume, in a glycerin-preserved extracting fluid, supplied in 5, 10, 30, and 50 mL vials. (3, 16) Refer to the vial label for the product concentration. (11)

4 CONTRAINDICATIONS

Non-standardized allergenic extracts are contraindicated in individuals with the following conditions:

- Severe, unstable or uncontrolled asthma.
- History of any severe systemic reaction to the allergen extract when administered for diagnosis or treatment.
- Medical conditions that reduce the ability to survive anaphylaxis.

5 WARNINGS AND PRECAUTIONS

5.1 Anaphylaxis

Anaphylaxis, which may lead to death, can occur in individuals following the administration of non-standardized allergenic extracts, particularly in the following situations:

- Extreme sensitivity to the non-standardized allergenic extract.
- Concomitant environmental exposure to allergens.
- Receipt of high doses of the non-standardized allergenic extract.
- Receipt of an accelerated build-up schedule (“rush” immunotherapy).
- Change from one lot of a particular non-standardized allergenic extract to another lot of the same non-standardized allergenic extract.

Administer non-standardized allergenic extracts in a healthcare setting under the supervision of a physician prepared to manage anaphylaxis; management may include use of inhaled bronchodilators and use of epinephrine. Non-standardized allergenic extracts may not be suitable for individuals who may be unresponsive to epinephrine or inhaled bronchodilators, such as those taking beta-blockers. See prescribing information for epinephrine for complete information, particularly on medications that blunt or potentiate epinephrine activity. Individuals should remain in the physician’s office for a minimum of 30 minutes after receiving an injection of non‑standardized allergenic extracts, so that any adverse reaction can be observed and properly handled.

5.2 Cross-reactions and Dose Sensitivity

When determining the final dose of an allergen mixture for immunotherapy, consider cross-reactivity among component extracts.

Determine the initial dilution of allergenic extract, starting dose, and progression of dosage based on the patient’s history and results of skin tests [see Dosage and Administration (2)]. Strongly positive skin tests can be indicators for potential adverse reactions.

6 ADVERSE REACTIONS

Common adverse reactions reported for non-standardized allergenic extracts are:

- Local reactions occurring in 26 to 82% of all patients who receive subcutaneous immunotherapy, at the injection site (e.g., erythema, swelling, pruritus, tenderness and pain).^2
- Systemic adverse reactions, occurring in ≤ 7% of patients who receive subcutaneous immunotherapy (e.g., generalized skin erythema, urticaria, pruritus, angioedema, rhinitis, wheezing, laryngeal edema, hypotension, and shock).^3 Systemic reactions may be fatal.^2

No clinical trials of non-standardized allergenic extracts have been conducted.

Published studies of non-standardized allergenic extracts report systemic reactions occurring in fewer than 1% in patients receiving conventional immunotherapy and greater than 36% in patients receiving rush immunotherapy. Most systemic reactions occurred within 30 minutes of injection. However, systemic reactions have been reported to occur up to 2 hours after the final injection with rush schedules. Some reactions have occurred up to 6 hours after skin tests or immunotherapy.^(2, 3)

7 DRUG INTERACTIONS

7.1 Antihistamines

Do not perform skin testing with non-standardized allergenic extracts within 3 to 10 days of first-generation H1-histamine receptor blockers (e.g., clemastine, diphenhydramine) and second-generation antihistamines (e.g., loratadine, fexofenadine) being used. These products suppress histamine skin test reactions and could mask a positive response.^(1, 2)

7.2 Topical Corticosteroids and Topical Anesthetics

Topical corticosteroids may suppress skin reactivity; therefore, discontinue use at the skin test site for at least 2 to 3 weeks before skin testing. Avoid use of topical local anesthetics at skin test sites because they can suppress flare responses.^(1, 2)

7.3 Tricyclic Antidepressants

Tricyclic antidepressants, such as doxepin, can have potent antihistamine effects and may alter skin test results. Allow 7 to 14 days after discontinuation of tricyclic medication prior to skin testing.^(1, 2)

8 USE IN SPECIFIC POPULATIONS

8.1 Pregnancy

Risk Summary

All pregnancies have a risk of birth defect, loss, or other adverse outcomes. In the U.S. general population, the estimated background risk of major birth defects and miscarriage in clinically recognized pregnancies is 2 to 4% and 15 to 20%, respectively. There are no human or animal data to establish the presence or absence of non-standardized allergenic extracts‑associated risks during pregnancy.

8.2 Lactation

Risk Summary

It is not known whether non-standardized allergenic extracts are present in human milk. Data are not available to assess the effects of these extracts on the breastfed child or on milk production/excretion. The developmental and health benefits of breastfeeding should be considered along with the mother’s clinical need for non-standardized allergenic extracts and any potential adverse effects on the breastfed child from the extracts or from the underlying maternal condition.

8.4 Pediatric Use

For use of these products in children younger than 5 years of age, consideration should be given to the patient’s ability to comply and cooperate with receipt of the product and the potential for difficulty in communicating with the child regarding systemic reactions.²

The volume of a dose for immunotherapy may need to be divided for pediatric patients [see Dosage and Administration (2.3)]

8.5 Geriatric Use

Data are not available to determine if subjects 65 years of age and older respond differently to allergen immunotherapy than younger subjects.

11 DESCRIPTION

Non-standardized allergenic extracts are labeled “No U.S. Standard of Potency”.

Non-standardized allergenic extracts are supplied in a Glycero Cocas extraction solution, which consists of 0.5% sodium chloride for isotonicity, 0.275% sodium bicarbonate as a buffer, and 50% glycerin (volume/volume) as preservative.

Non-standardized allergenic extracts are supplied as a weight to volume (w/v) solution of allergen in extraction solution. Product concentrations vary based on the source. Refer to the vial label for the product concentration.

Source material mold mycelia and Candida albicans cells are cultivated on liquid medium which may contain one or more of the following constituents: casein hydrolysate; malt extract; yeast extract; maltose; dextrose; ammonium nitrate, calcium carbonate, calcium chloride, ammonium citrate, potassium phosphate, sodium citrate, citric acid; magnesium sulfate; or trace elements. Acetone and ether may be used as drying and de-fatting agents. Candida albicans cells are treated with phenol, which is removed by dialysis.

Dog Hair and Dander extracts are manufactured in 3 product forms:

- Dog Hair and Dander (Regular Process) is derived from extraction of the source material without additional processing, and is prepared at 1:10 w/v in Glycero-Cocas.
- Acetone Precipitated (AP) Dog Hair and Dander is derived from the acetone precipitated aqueous extract and is prepared at 1:100 w/v in Glycero-Cocas.
- Ultrafiltered (UF) Dog Hair and Dander is derived from the UF aqueous extract and is prepared at 1:650 w/v in Glycero‑Cocas.

12 CLINICAL PHARMACOLOGY

12.1 Mechanism of Action

The skin test reaction results from interaction of the introduced allergen and allergen-specific IgE antibodies bound to mast cells, leading to mast cell degranulation and release of histamine, tryptase and other mediators, which results in the formation of the wheal and flare.

The precise mechanisms of action of allergen immunotherapy are not known. Immunologic responses to immunotherapy include changes in allergen-specific IgE levels, allergen-specific IgG levels, and regulatory T cell responses.^2

14 CLINICAL STUDIES

Specific immunotherapy with allergenic extracts is helpful in reducing symptoms associated with exposure to the offending allergens. A summary of effectiveness by the Panel on Review of Allergenic Extracts, an advisory committee to the U.S. Food and Drug Administration, has been published.^5

15 REFERENCES

1. Bernstein IL, Li JT, Bernstein Dl, et al. Allergy diagnostic testing: and updated practice parameter. Ann Allergy Asthma Immunol. 2008 Mar;100:S1-148.

2. Cox L, Nelson H, Lockey R, Calabria C, Chacko T, Finegold I, et al. Allergen immunotherapy: A practice parameter third update. J Allergy Clin Immunol. 2011 Jan;127:S1-55.

3. Greineder DK. Risk management in allergen immunotherapy. J Allergy Clin Immunol. 1996 Dec;98(6 Pt 3):S330-4

4. Golden D B K, Demain J, Freeman T, Graft D, et al. Stinging insect hypersensitivity: A practice parameter update 2016. Ann Allergy Asthma Immunol 118 (2017) 28-54.

5. Federal Register Proposed Rule: Biological Products: Implementation of Efficacy Review, Allergenic Extracts, Federal Register 1985;50:3082-3288.

16 HOW SUPPLIED

Non-standardized allergenic extracts and mixes are supplied as 50% glycerin stock concentrates labeled in weight/volume and provided in 10 milliliter, 30 milliliter and 50 milliliter vials for use in percutaneous skin testing and subcutaneous immunotherapy. These extracts may also be supplied in 5 milliliter dropper vials for percutaneous testing only.

These products are supplied as listed in Table 2.

TABLE 2: AVAILABLE PRODUCTS

POLLEN – GRASS ALLERGENS

Bahia Grass,Paspalum notatum

Brome, SmoothBromus inermis

Corn, CultivatedZea mays

Grass Mix 8-100,000 BAU/mL each ofP. pratensis; A. gigantean; P. pretense;10,000 BAU/mL ofC. dactylon; 1:20w/v ofS. halepense

Johnson Grass,Sorghum halepense

Oats, Common Cultivated,Avena sativa

POLLEN – TREE ALLERGENS

Acacia, Golden,Acacia longifolia

Alder, Red,Alnus rubra

Ash, White,Fraxinus americana

Beech, American,Fagus grandifolia

Birch Mix (PRW)-B. papyrifera, B. pendula, B. nigra

Bottlebrush,Melaleuca citrina

Boxelder/Maple Mix (BHR)-A. negundo, A. saccharum, A. rubrum

Cedar, Mountain,Juniperus ashei

Cedar, Red,Juniperus virginiana

Cottonwood, Common,Populus deltoides

Cyprus, Arizona,Cupressus arizonica

Cyprus, Bald,Taxodium distichum

Elm, American,Ulmus americana

Elm, Chinese,Ulmus parvifolia

Gum, Sweet,Liquidambar styraciflua

Hackberry,Celtis occidentalis

Hickory, Shagbark,Carya ovata

Maple, Hard/Sugar,Acer saccharum

Melaleuca,Melaleuca quinquenervia

Mesquite,Prosopis glandulosa

Mulberry Mix (RW)-M. rubra, M. alba

Oak Mix (RVW)-Q. rubra, Q. virginiana, Q. alba

Oak, Red,Quercus Rubra

Olive Tree,Olea europaea

Palm, Queen,Syagrus romanzoffiana

Pecan Tree,Carya illinoinensis

Pine Mix (LY)-P. contorta, P. ponderosa

Privet, Common,Ligustrum vilgare

Russian Olive,Elaeagnus angustifolia

Sycamore, American,Platanus occidentalis

Tree Mix 5-20% each ofF. Americana; J. nigra; P. deltoides; U. Americana;6.7% each ofB. papyrifera; B. nigra; B. pendula

Tree Mix 6- Tree Mix 6-20% each ofF. Americana; J. nigra; P. deltoides; U. Americana;6.7% each ofB. papyrifera; B. nigra; B. pendula

Tree Mix 11-10% each ofF. americana; B. nigra; J. nigra; P. deltoides; U. americana; C. ovata; A. saccharum; Q. rubra; P. occidentalis; S. nigra

Walnut, Black,Juglans nigra

Willow, Black,Salix nigra

POLLEN – WEED AND GARDEN PLANT ALLERGENS

Careless Weed,Amaranthus palmeri

Careless/Pigweed Mix (CR)-A. palmeri, A. retroflexus

Cocklebur, Common,Xanthium strumarium

Dock/Sorrel Mix (DS)-R. crispus, R. acetosella

Dog Fennel, Eastern,Eupatorium capillifolium

Goldenrod,Solidago canadensis

Kochia,Kochia scoparia

Lamb’s Quarters,Chenopodium album

Marshelder/Poverty Mix (BPT)-C. xanthifolia, I. annua, I. axillaris

Nettle,Urtica dioica

Pigweed, Rough Redroot,Amaranthus retroflexus

Plantain, English,Plantago lanceolata

Ragweed, Giant,Ambrosia trifida

Ragweed Mix (GSW)-A. trifida, A. artemisiifolia, A. psilostachya

Ragweed, Western,Ambrosia psilostachya

Russian Thistle,Salcola kali

Sagebrush, Mugwort,Artemisia vulgaris

Scale, Wing,Atriplex canescens

Sorrel, Sheep,Rumex acetosella

Weed Mix 2630-25% each ofX. strumarium; C. album; A. retroflexus;12.5% each ofR. crispus; R. acetosella

MOLDS

Alternaria/Hormodendrum Mix-A. tenuis, H. cladosporioides

Alternaria tenuis (Alternariaalternata)

Aspergillus fumigatus

Aspergillus niger var. niger

Botrytis cinerea

Candida albicans

Cephalosporium acremonium (Sarocladiumstrictum)

Curvularia spicifera (Cochliobolusspicifer)

Epicoccum nigrum

Epidermophyton floccosum

Fusarium vasinfectum (Fusariumoxysporumvasinfectum)

Heliminthosporium interseminatum (Dendryphiellavinosa)

Hormodendrum cladosporioides (Cladosporium cladosporioides)

Mold Mix 4-25% each ofA. alternata; C. cladosporioides;6.2% each ofA. fumigatus; A. nidulans; A. nigervar. niger; A. terreus; P. digitatum; P. expansum; P. chrysogenumvar. chrysogenum; C. rosea f. rosea

Mold Mix 10-2.5% each ofA. fumigatus; A. nidulans; A. nigervar. niger; A. terreus; P. digitatum; P. expansum; P. chrysogenumvar. chrysogenum; C. roseaf. rosea;10% each ofA. alternata; F. oxysporumvasinfectum; D. vinosa; C. cladosporioides; M. racemosus; P. exiguavar. exigua; A. pullulansvar. pullutans; R. stolonifer

Mucor racemosus

Penicillium Mix-P. expansum, P. digitatum, P. chrysogenum, C. rosea

Penicillium notatum (Penicilliumchrysogenumvar. chrysogenum)

Phoma herbarum (Phomaexiguavar. exigua)

Pullularia pullulans (Aerobasidiumpullulansvar. pullulans)

Rhizopus nigricans (Rhizopusstolonifer)

Stemphylium botryosum (Pleosporatarda)

Trichophyton Mix-T. tonsurans, T. rubrum , T. mentagrophytes

EPIDERMALS

AP Horse Hair and Dander,Equuscaballus

AP Cattle Hair and Dander,Bostaurus

AP Dog Hair and Dander,Canislupusfamiliaris

Dog Hair and Dander,Canislupusfamiliaris

UF Dog Hair and Dander,Canislupusfamiliaris

Feather Mix-G. gallus, A. platyrhynchos, A. anser

Guinea Pig Hair and Dander,Caviaporcellus

INSECTS

Cockroach, American,Periplanetaamericana

Cockroach, German,Blatellagermanica

Cockroach Mix-P. americana, B. germanica

Fire Ant,Solenopsisinvicta

16.2 Storage and Handling

Store extracts at 2°C to 8°C (36°F to 46°F).

17 PATIENT COUNSELING INFORMATION

Instruct patients to remain in the office under observation for a minimum of 30 minutes after an injection or longer, if deemed necessary for the individual.

Inform patients that reactions may occur more than 30 minutes after skin testing or an injection.

Instruct patient to recognize the following symptoms as systemic adverse reactions and seek emergency medical care right away if any of these symptoms occur:

- Unusual swelling and/or tenderness at the injection site.
- Hives or itching of the skin.
- Swelling of face and/or mouth.
- Sneezing, coughing, or wheezing.
- Shortness of breath.
- Nausea.
- Dizziness or faintness.

Manufacturer:

Jubilant HollisterStier LLC

Spokane, WA 99207 U.S.A.

U.S. Lic. No. 1272

Version Date: February 24, 2022

PRINCIPAL DISPLAY PANEL

UF Dog Hair-Dander, 10 mL 1.650wv Carton Label
UF Dog Hair-Dander, 10 mL 1.650wv Vial Label